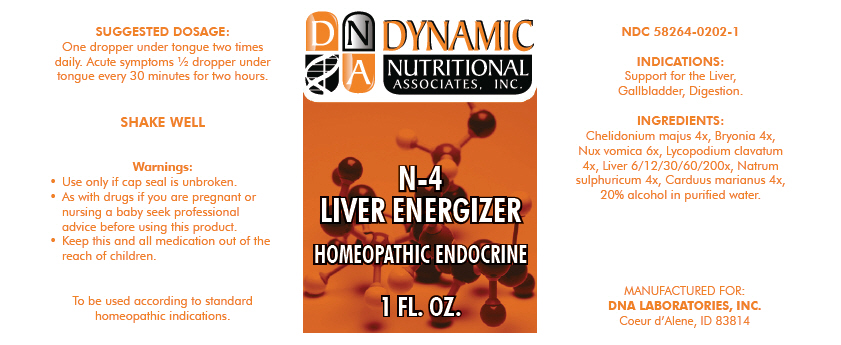 DRUG LABEL: N-4
NDC: 58264-0202 | Form: SOLUTION
Manufacturer: DNA Labs, Inc.
Category: homeopathic | Type: HUMAN OTC DRUG LABEL
Date: 20250109

ACTIVE INGREDIENTS: CHELIDONIUM MAJUS 4 [hp_X]/1 mL; BRYONIA ALBA ROOT 4 [hp_X]/1 mL; STRYCHNOS NUX-VOMICA SEED 6 [hp_X]/1 mL; LYCOPODIUM CLAVATUM WHOLE 4 [hp_X]/1 mL; MAMMAL LIVER 200 [hp_X]/1 mL; SODIUM SULFATE 4 [hp_X]/1 mL; MILK THISTLE 4 [hp_X]/1 mL
INACTIVE INGREDIENTS: ALCOHOL; WATER

N-4

NDC 58264-0202-1

INDICATIONS

PURPOSE

Support for the Liver, Gallbladder, Digestion.

INGREDIENTS

INACTIVE INGREDIENT

Chelidonium majus 4x, Bryonia 4x, Nux vomica 6x, Lycopodium clavatum 4x, Liver 6/12/30/60/200x, Natrum sulphuricum 4x, Carduus marianus 4x, 20% alcohol in purified water.

SUGGESTED DOSAGE

One dropper under tongue two times daily. Acute symptoms ½ dropper under tongue every 30 minutes for two hours.

STORAGE AND HANDLING

SHAKE WELL

Warnings

- Use only if cap seal is unbroken.

PREGNANCY OR BREAST FEEDING

- As with drugs if you are pregnant or nursing a baby seek professional advice before using this product.

KEEP OUT OF REACH OF CHILDREN

- Keep this and all medication out of the reach of children.

To be used according to standard homeopathic indications.

PRINCIPAL DISPLAY PANEL - 1 FL. OZ. Bottle Label

DYNAMIC
NUTRITIONAL
ASSOCIATES, INC.

N-4
LIVER ENERGIZER

HOMEOPATHIC ENDOCRINE

1 FL. OZ.